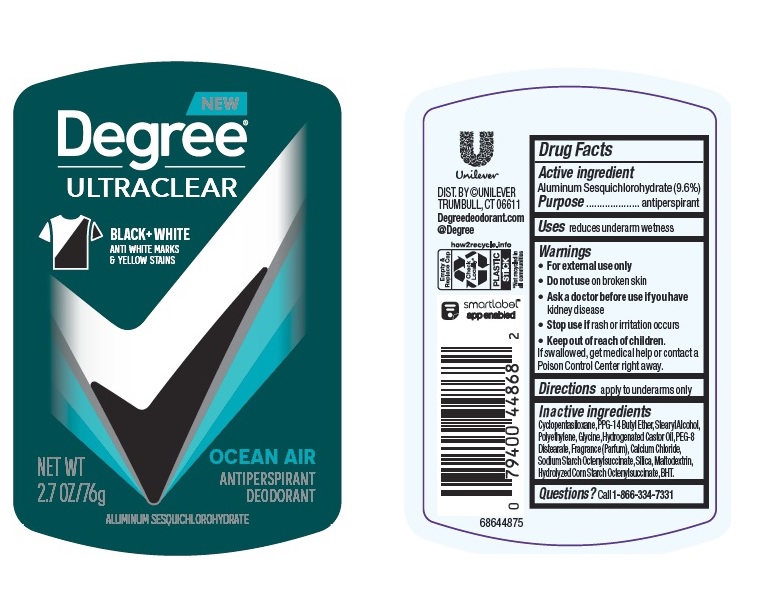 DRUG LABEL: Degree
NDC: 64942-1957 | Form: STICK
Manufacturer: Conopco Inc. d/b/a/ Unilever
Category: otc | Type: HUMAN OTC DRUG LABEL
Date: 20241108

ACTIVE INGREDIENTS: ALUMINUM SESQUICHLOROHYDRATE 9.6 g/100 g
INACTIVE INGREDIENTS: GLYCINE; HYDROGENATED CASTOR OIL; CALCIUM CHLORIDE; CYCLOMETHICONE 5; BUTYLATED HYDROXYTOLUENE; HIGH DENSITY POLYETHYLENE; PEG-8 DISTEARATE; MALTODEXTRIN; PPG-14 BUTYL ETHER; STEARYL ALCOHOL; SILICON DIOXIDE

Degree Ultraclear Black + White Ocean Air Antiperspirant Deodorant

Drug Facts

Active ingredient

Aluminum Sesquichlorohydrate (9.6%)

Purpose

antiperspirant

Uses

reduces underarm wetness

Warnings

• For external use only.
• Do not use on broken skin .
• Ask a doctor before use if you have kidney disease.
• Stop use if rash or irritation occurs.

• Keep out of reach of children.

If swallowed, get medical help or contact a Poison Control Center right away.

Directions

apply to underarms only

Inactive ingredients

Cyclopentasiloxane, PPG-14 Butyl Ether, Stearyl Alcohol, Polyethylene, Glycine, Hydrogenated Castor Oil, PEG-8 Distearate, Fragrance (Parfum), Calcium Chloride, Sodium Starch Octenylsuccinate, Silica, Maltodextrin, Hydrolyzed Corn Starch Octenylsuccinate, BHT.

Questions?

Call toll-free 1-866-334-7331